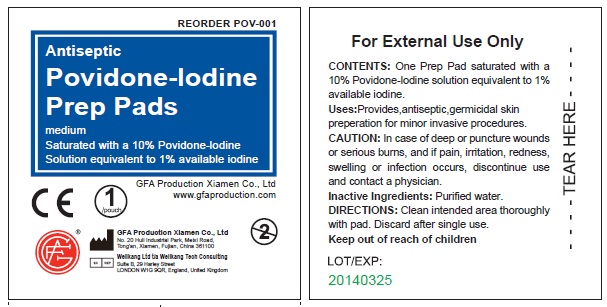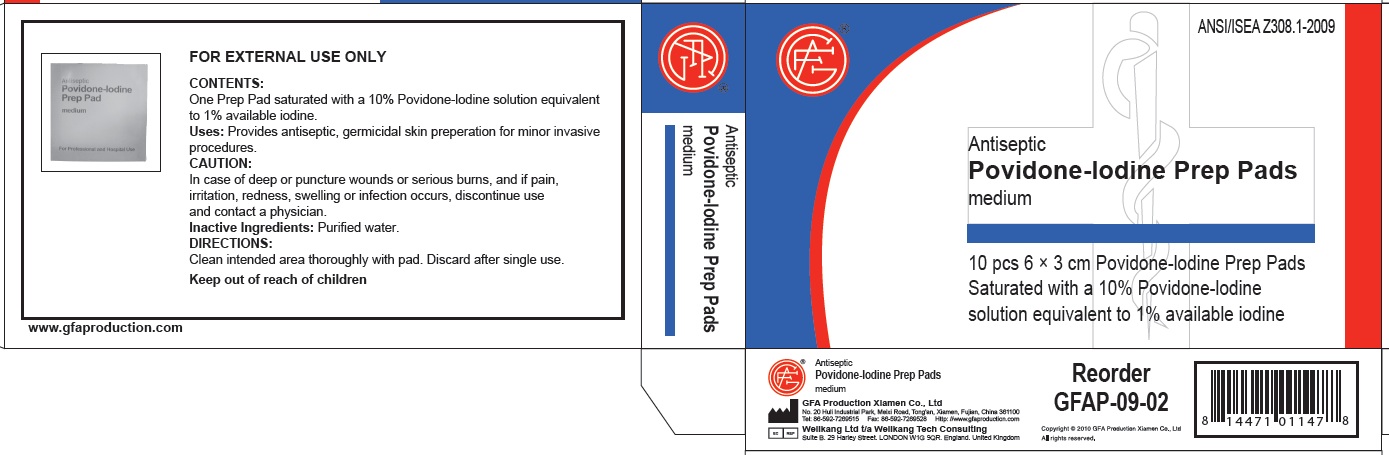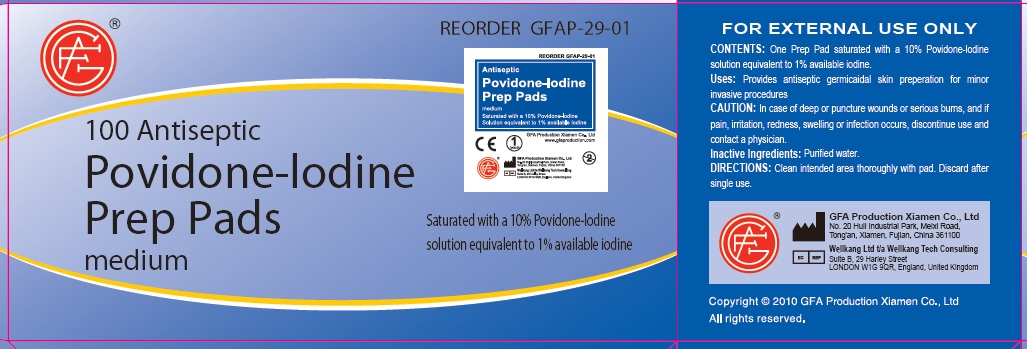 DRUG LABEL: Povidone-Iodine Prep
NDC: 52124-2901 | Form: SWAB
Manufacturer: Genuine First Aid, LLC
Category: otc | Type: HUMAN OTC DRUG LABEL
Date: 20110405

ACTIVE INGREDIENTS: POVIDONE-IODINE 1 mL/100 mL
INACTIVE INGREDIENTS: WATER

Povidone-Iodine Prep Pads

Active Ingredient

One Prep pad saturated with a 10% Povidone-Iodine solution equivalent to 1% available iodine

Purpose

antiseptic, germicidal

Uses

Provides, antiseptic germicidal skin preperation for minor invasive procedures

Keep out of reach of children

For external use only.

Caution

In case of deep or puncture wounds or serious burns, and if pain, irritation, redness, swelling or infection occurs, discontinue use and contact a physician.

Inactive Ingredients

Purified water.

Directions

Clean intended area thoroughly with pad. Discard after single use.

PACKAGE LABEL

Antiseptic
Povidone-Iodine
Prep Pads
medium
Saturated with a 10% Povidone-Iodine
Solution equavalent to 1% available iodine
GFA Production Xiamen Co., Ltd.
www.gfaproduction.com
GFA Production Xiamen Co., Ltd.
No. 20 Huli Industrial Park, Meixi Road,
Tong'an, Xiamen, Fujian, China 361100
Wellkang Ltd t/a Wellkang Tech Consulting
Suite B, 29 Harley Street
LONDON W1G 9QR, England, United Kingdom